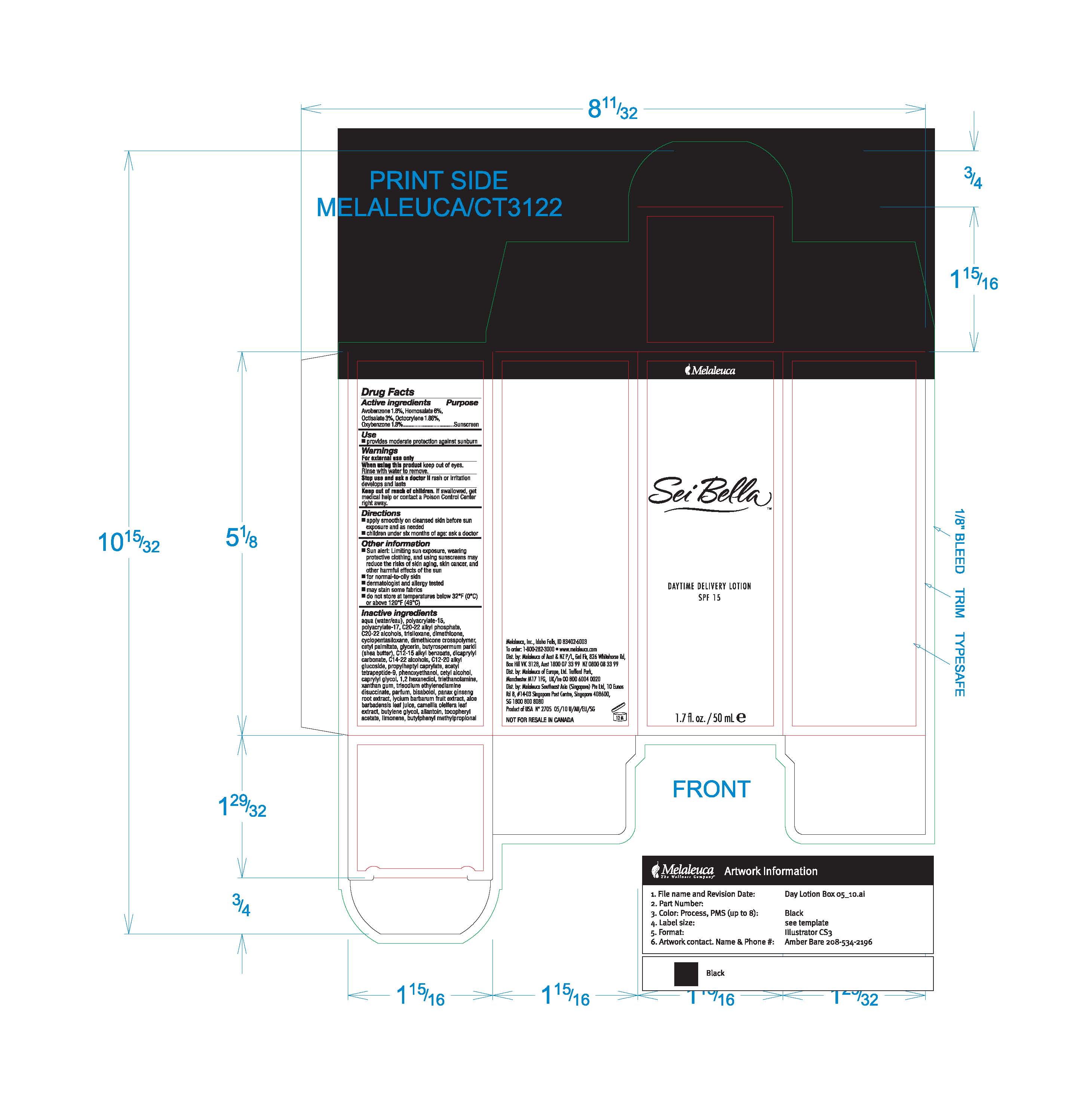 DRUG LABEL: Sei Bella
NDC: 54473-187 | Form: LOTION
Manufacturer: Melaleuca, Inc.
Category: otc | Type: HUMAN OTC DRUG LABEL
Date: 20110203

ACTIVE INGREDIENTS: AVOBENZONE 0.9018 g/50 mL; HOMOSALATE 3.006 g/50 mL; OCTISALATE 1.503 g/50 mL; OCTOCRYLENE 0.9319 g/50 mL; Oxybenzone 0.9018 g/50 mL
INACTIVE INGREDIENTS: Water; TRISILOXANE; DIMETHICONE; Cyclomethicone 5; CETYL PALMITATE; Glycerin; SHEA BUTTER; C12-15 ALKYL BENZOATE; DICAPRYLYL CARBONATE; C14-22 ALCOHOLS; PHENOXYETHANOL; Cetyl Alcohol; CAPRYLYL GLYCOL; Trolamine; XANTHAN GUM; LEVOMENOL; ALOE VERA LEAF; CAMELLIA OLEIFERA LEAF; BUTYLENE GLYCOL; ALLANTOIN; ALPHA-TOCOPHEROL ACETATE; ASIAN GINSENG

Sei Bella Daytime Delivery Lotion Content of Label

Active ingredients
Avobenzone 1.8%, Homosalate 6%, Octisalate 3%, Octocrylene 1.86%, Oxybenzone 1.8%

Purpose
Sunscreen

Use

- provides moderate protection against sunburn

Warnings
Foe external use only

When using this product keep out of eyes. Rinse with water to remove.

Stop use and ask a doctor if rash or irritation develops and lasts.

Keep out of reach of children. If swallowed, get medical help or contact a Poison Control Center right away.

Directions

- apply smoothly on cleansed skin before sun exposure and as needed
- children under six months or age: ask a doctor

Other information

- Sun alert: Limiting sun exposure, wearing protective clothing, and using sunscreens may reduce the risks of skin aging, skin cancer, and other harmful effects of the sun
- may stain some fabrics

Other information

- dermatologist and allergy tested

Other information

- do not store at temperatures below 32°F (0°C) or above 120°C (49°C)

Inactive ingredients
aqua (water/eau), polyacrylate-15, polyacrylate-17, C20-22 phosphate, C20-22 alcohols, trisiloxane, dimethicone, cyclopentasiloxane, dimethicone crosspolymer, cetyl palmitate, glycerin, butyrospermum parkii (shea butter), C12-15 alkyl benzoate, dicaprylyl carbonate, C14-22 alcohols, C12-20 alkyl glucoside, propylheptyl caprylate, acetyl tetrapeptide-9, phenoxyethanol, cetyl alcohol, caprylyl glycol, 1,2 hexanediol, triethanolamine, xanthan gum, trisodium ethylenediamine disuccinate, parfum, bisabolol, panax ginseng root extract, lycium barbarum fruit extract, aloe barbadensis leaf juice, camellia oleifera leaf extract, butylene glycol, allantoin, tocopheryl acetate, limonene, butylphenyl methylpropional